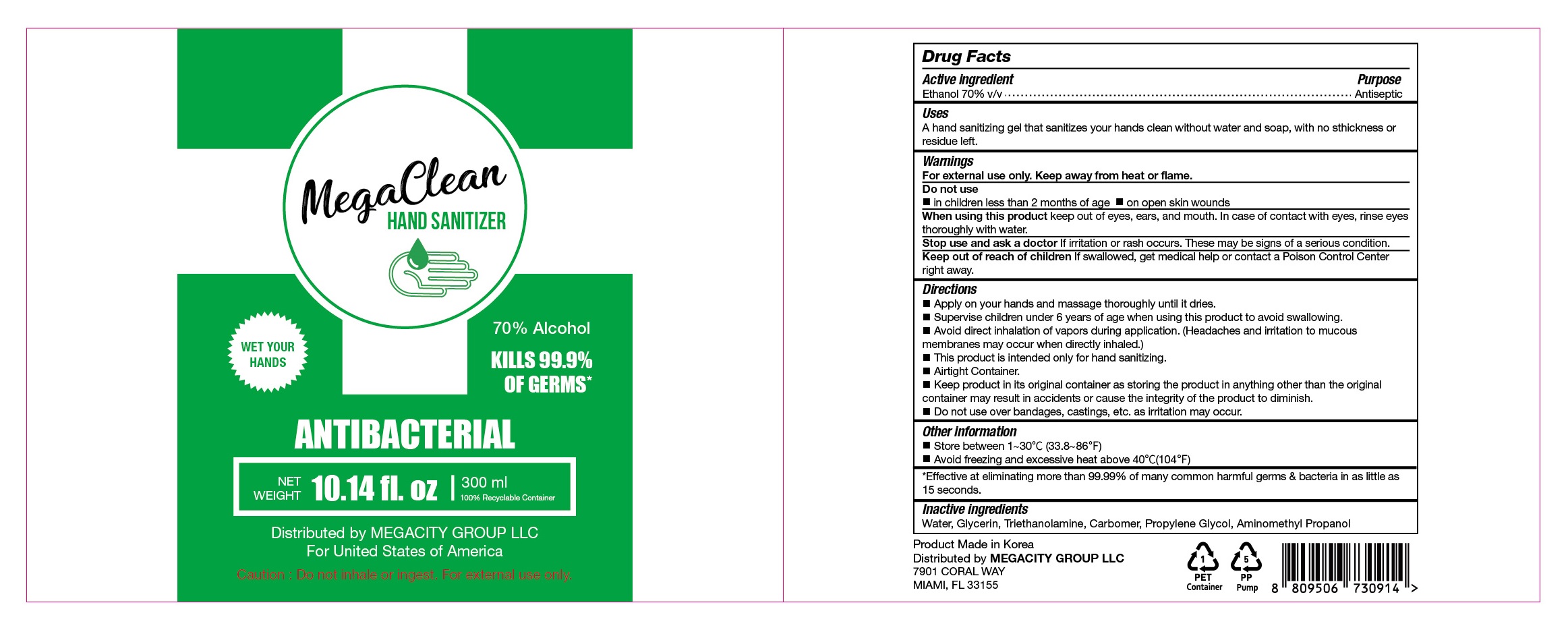 DRUG LABEL: MegaClean HAND SANITIZER
NDC: 77799-370 | Form: GEL
Manufacturer: MEGACITY GROUP LLC
Category: otc | Type: HUMAN OTC DRUG LABEL
Date: 20200531

ACTIVE INGREDIENTS: ALCOHOL 210 mL/300 mL
INACTIVE INGREDIENTS: AMINOMETHYLPROPANOL; GLYCERIN; WATER; PROPYLENE GLYCOL; TROLAMINE; CARBOMER HOMOPOLYMER, UNSPECIFIED TYPE

MegaClean HAND SANITIZER 300 mL
77799-370-01